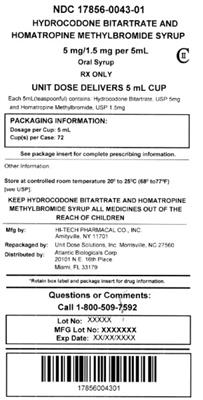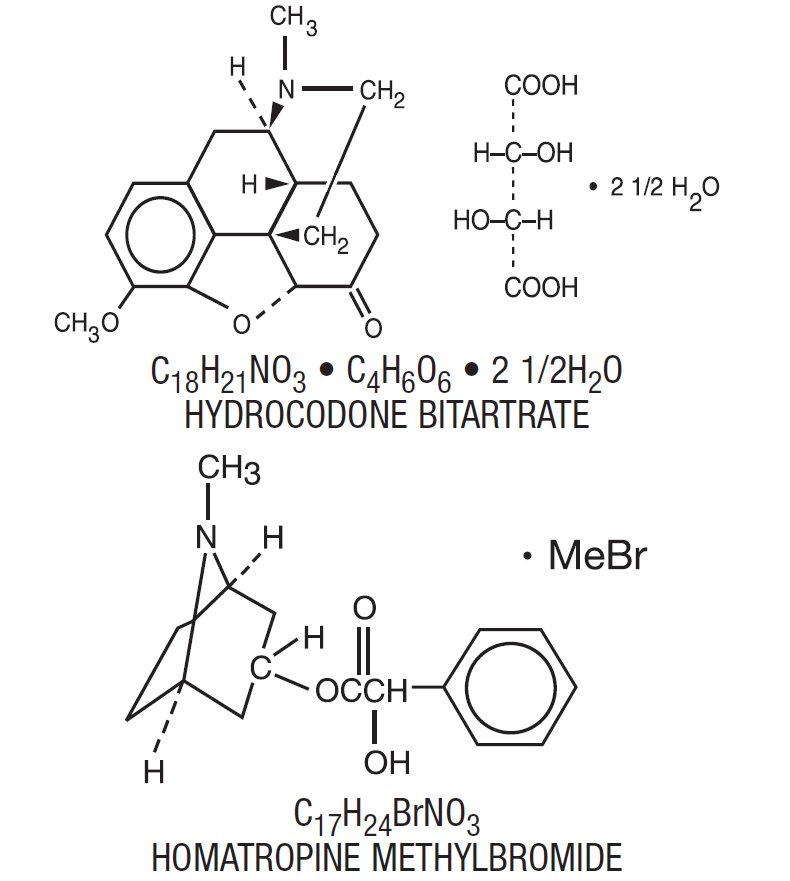 DRUG LABEL: Hydrocodone Bitartrate and Homatropine Methylbromide
NDC: 17856-0043 | Form: SYRUP
Manufacturer: Atlantic Biologicals Corps
Category: prescription | Type: HUMAN PRESCRIPTION DRUG LABEL
Date: 20160301
DEA Schedule: CII

ACTIVE INGREDIENTS: HYDROCODONE BITARTRATE 5 mg/5 mL; HOMATROPINE METHYLBROMIDE 1.5 mg/5 mL
INACTIVE INGREDIENTS: ANHYDROUS CITRIC ACID; CARAMEL; CHERRY; FD&C RED NO. 40; METHYLPARABEN; PROPYLPARABEN; SODIUM CITRATE; SORBITOL; SUCROSE; WATER

HYDROCODONE BITARTRATE AND HOMATROPINE METHYLBROMIDE SYRUP

DESCRIPTION

This product contains hydrocodone (dihydrocodeinone) bitartrate, a semisynthetic centrally-acting narcotic antitussive. Homatropine methylbromide is included in a subtherapeutic amount to discourage deliberate overdosage.

Each teaspoonful (5 mL) for oral administration contains:

Hydrocodone Bitartrate, USP 5 mg

WARNING: May be habit forming.

Homatropine Methylbromide, USP 1.5 mg

Hydrocodone Bitartrate and Homatropine Methylbromide Syrup also contains: Caramel color, cherry flavor, citric acid, FD&C Red #40, methylparaben, propylparaben, purified water, sorbitol solution and sucrose syrup. Citric acid and/or sodium citrate may be added to adjust pH.

The hydrocodone component is a 4,5α-epoxy-3- methoxy-17-methylmorphinan-6-one tartrate (1:1) hydrate (2:5), a fine white crystal or crystalline powder, which is derived from the opium alkaloid, thebaine, has a molecular weight of (494.50) and may be represented by the following structural formula:

Homatropine methylbromide is 8-Azoniabicyclo [3.2.1]octane,3-[(hydroxy-phenylacetyl)oxy]-8, 8-dimethyl-,bromide,endo-; a white crystal or fine white crystalline powder, with a molecular weight of (370.29).

CLINICAL PHARMACOLOGY

Hydrocodone is a semisynthetic narcotic antitussive and analgesic with multiple actions qualitatively similar to those of codeine. The precise mechanism of action of hydrocodone and other opiates is not known; however, hydrocodone is believed to act directly on the cough center. In excessive doses, hydrocodone, like other opium derivatives, will depress respiration. The effects of hydrocodone in therapeutic doses on the cardiovascular system are insignificant. Hydrocodone can produce miosis, euphoria, physical and physiological dependence.

Following a 10 mg oral dose of hydrocodone administered to five adult male subjects, the mean peak concentration was 23.6 ± 5.2 ng/mL. Maximum serum levels were achieved at 1.3 ± 0.3 hours and the half-life was determined to be 3.8 ± 0.3 hours. Hydrocodone exhibits a complex pattern of metabolism including O-demethylation, N-demethylation and 6-keto reduction to the corresponding 6-α-and 6-β-hydroxymetabolites.

INDICATIONS AND USAGE

Hydrocodone bitartrate and homatropine methylbromide syrup is indicated for the symptomatic relief of cough.

CONTRAINDICATIONS

Hydrocodone bitartrate and homatropine methylbromide syrup should not be administered to patients who are hypersensitive to hydrocodone or homatropine methylbromide.

WARNINGS

May be habit forming. Hydrocodone can produce drug dependence of the morphine type and, therefore, has the potential for being abused. Psychic dependence, physical dependence and tolerance may develop upon repeated administration of hydrocodone bitartrate and homatropine methylbromide and it should be prescribed and administered with the same degree of caution appropriate to the use of other narcotic drugs (see). DRUG ABUSE AND DEPENDENCE

Head Injury and Increased Intracranial Pressure

The respiratory depression properties of narcotics and their capacity to elevate cerebrospinal fluid pressure may be markedly exaggerated in the presence of head injury, other intracranial lesions or a pre-existing increase in intracranial pressure. Furthermore, narcotics produce adverse reactions which may obscure the clinical course of patients with head injuries.

Acute Abdominal Conditions

The administration of hydrocodone bitartrate and homatropine methylbromide or other narcotics may obscure the diagnosis or clinical course of patients with acute abdominal conditions.

Pediatric Use

In young pediatric patients, as well as adults, the respiratory center is sensitive to the depressant action of narcotic cough suppressants in a dose-dependent manner. Benefit to risk ratio should be carefully considered especially in the pediatric population with respiratory embarrassment (e.g., croup).

PRECAUTIONS

General

Before prescribing medication to suppress or modify cough, it is important to ascertain that the underlying cause of cough is identified, that modification of cough does not increase the risk of clinical or physiological complications, and that appropriate therapy for the primary disease is provided.

Special Risk Patients

Hydrocodone bitartrate and homatropine methylbromide should be given with caution to certain patients such as the elderly or debilitated, and those with severe impairment of hepatic or renal functions, hypothyroidism, Addison’s disease, prostatic hypertrophy or urethral stricture, asthma, and narrow-angle glaucoma.

Information for Patients

Hydrocodone may impair the mental and/or physical abilities required for the performance of potentially hazardous tasks such as driving a car or operating machinery. The patient using hydrocodone bitartrate and homatropine methylbromide should be cautioned accordingly.

Drug Interactions

Patients receiving narcotics, antihistamines, antipsychotics, antianxiety agents or other CNS depressants (including alcohol) concomitantly with hydrocodone bitartrate and homatropine methylbromide may exhibit an additive CNS depression. When combined therapy is contemplated, the dose of one or both agents should be reduced. The use of MAO inhibitors or tricyclic antidepressants with hydrocodone preparations may increase the effect of either the antidepressant or hydrocodone.

Carcinogenesis, Mutagenesis, Impairment of Fertility

Studies of hydrocodone bitartrate and homatropine methylbromide in animals to evaluate the carcinogenic and mutagenic potential and the effect on fertility have not been conducted.

Pregnancy

: Pregnancy Category C: Animal reproduction studies have not been conducted with hydrocodone bitartrate and homatropine methylbromide. It is also not known whether hydrocodone bitartrate and homatropine methylbromide can cause fetal harm when administered to a pregnant woman or can affect reproduction capacity. Hydrocodone bitartrate and homatropine methylbromide should be given to a pregnant woman only if clearly needed. Teratogenic Effects

: Nonteratogenic Effects

Babies born to mothers who have been taking opioids regularly prior to delivery will be physically dependent. The withdrawal signs include irritability and excessive crying, tremors, hyperactive reflexes, increased respiratory rate, increased stools, sneezing, yawning, vomiting and fever. The intensity of the syndrome does not always correlate with the duration of maternal opioid use or dose.

Labor and Delivery

As with all narcotics, administration of hydrocodone bitartrate and homatropine methylbromide to the mother shortly before delivery may result in some degree of respiratory depression in the newborn, especially if higher doses are used.

Nursing Mothers

It is not known whether this drug is excreted in human milk. Because many drugs are excreted in human milk and because of the potential for serious adverse reactions in nursing infants from hydrocodone bitartrate and homatropine methylbromide, a decision should be made whether to discontinue nursing or to discontinue the drug, taking into account the importance of the drug to the mother.

Pediatric Use

Safety and effectiveness of hydrocodone bitartrate and homatropine methylbromide in pediatric patients under six have not been established.

ADVERSE REACTIONS

To report SUSPECTED ADVERSE REACTIONS, contact Hi-Tech Pharmacal Co., Inc. at 1-800-262-9010 or FDA at 1-800-FDA-1088 or www.fda.gov/medwatch.

Central Nervous System

Sedation, drowsiness, mental clouding, lethargy, impairment of mental and physical performance, anxiety, fear, dysphoria, dizziness, psychic dependence, mood changes.

Gastrointestinal System

Nausea and vomiting may occur; they are more frequent in ambulatory than in recumbent patients. Prolonged administration of hydrocodone bitartrate and homatropine methylbromide may produce constipation.

Genitourinary System

Ureteral spasm, spasm of vesicle sphincters and urinary retention have been reported with opiates.

Respiratory System

Hydrocodone bitartrate and homatropine methylbromide may produce dose-related respiratory depression by acting directly on brain stem respiratory centers (see). OVERDOSAGE

Dermatological

Skin rash, pruritus.

DRUG ABUSE AND DEPENDENCE

Hydrocodone bitartrate and homatropine methylbromide syrup is a Schedule II narcotic. Psychic dependence, physical dependence and tolerance may develop upon repeated administration of narcotics; therefore, hydrocodone bitartrate and homatropine methylbromide should be prescribed and administered with caution. However, psychic dependence is unlikely to develop when hydrocodone bitartrate and homatropine methylbromide is used for a short time for the treatment of cough. Physical dependence, the condition in which continued administration of the drug is required to prevent the appearance of a withdrawal syndrome, assumes clinically significant proportions only after several weeks of continued oral narcotic use, although some mild degree of physical dependence may develop after a few days of narcotic therapy.

OVERDOSAGE

Signs and Symptoms

Serious overdosage with hydrocodone is characterized by respiratory depression (a decrease in respiratory rate and/or tidal volume, Cheyne-Stokes respiration, cyanosis), extreme somnolence progressing to stupor or coma, skeletal muscle flaccidity, cold and clammy skin, and sometimes bradycardia and hypotension. In severe overdosage, apnea, circulatory collapse, cardiac arrest and death may occur. The ingestion of very large amounts of hydrocodone bitartrate and homatropine methylbromide may, in addition, result in acute homatropine intoxication.

Treatment

Primary attention should be given to the reestablishment of adequate respiratory exchange through provision of a patent airway and the institution of assisted or controlled ventilation. The narcotic antagonist naloxone hydrochloride is a specific antidote for respiratory depression which may result from overdosage or unusual sensitivity to narcotics including hydrocodone. Therefore, an appropriate dose of naloxone hydrochloride should be administered, preferably by the intravenous route, simultaneously with efforts at respiratory resuscitation. For further information, see full prescribing information for naloxone hydrochloride. An antagonist should not be administered in the absence of clinically significant respiratory depression. Oxygen, intravenous fluids, vasopressors and other supportive measures should be employed as indicated. Gastric emptying may be useful in removing unabsorbed drug.

DOSAGE AND ADMINISTRATION

Adults

One (1) teaspoonful (5 mL) of the syrup every 4 to 6 hours as needed; do not exceed six (6) teaspoonfuls in 24 hours.

Children 6 to 12 Years of Age

One-half (1/2) teaspoonful (2.5 mL) of the syrup every 4 to 6 hours as needed; do not exceed three (3) teaspoonfuls in 24 hours.

HOW SUPPLIED

NDC:17856-0043-1 5 mL in a CUP, UNIT-DOSE